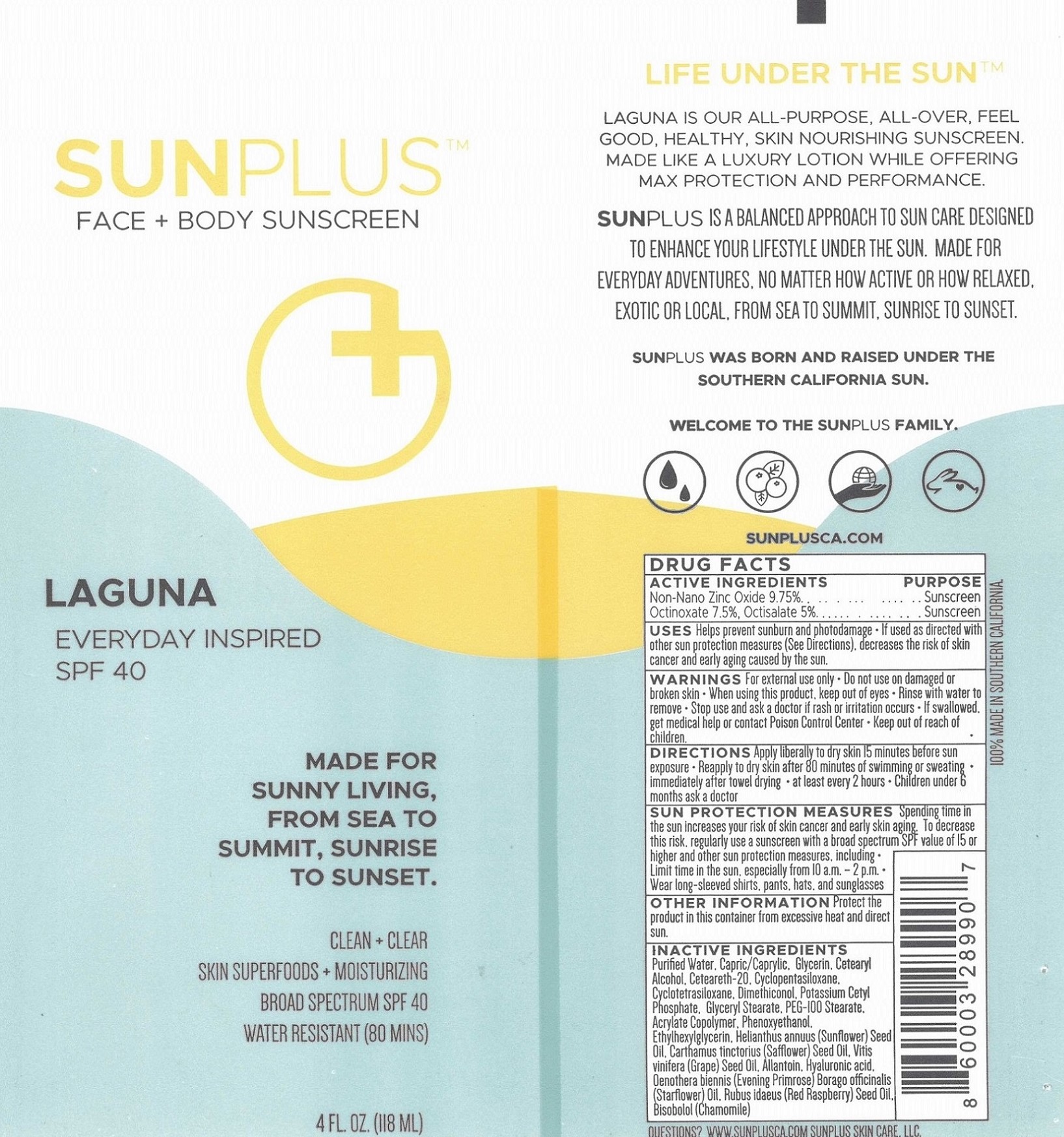 DRUG LABEL: Sunplus Sunscreen Laguna
NDC: 65112-263 | Form: LOTION
Manufacturer: I Shay Cosmetics Inc
Category: otc | Type: HUMAN OTC DRUG LABEL
Date: 20210127

ACTIVE INGREDIENTS: OCTINOXATE 7.5 g/100 g; OCTISALATE 5 g/100 g; ZINC OXIDE 9.75 g/100 g
INACTIVE INGREDIENTS: WATER 51.4 g/100 g

Sunplus Face + Body Sunscreen Laguna SPF 40

ACTIVE INGREDIENT

ZINC OXIDE 9.75%, OCTINOXATE 7.5%, OCTISALATE 5%

PURPOSE

Helps prevent sunburn and photodamage - If used as directed with other sun protection measures (See Directions). decreases the risks of skin cancer and early aging caused by the sun.

WARNINGS

For external use only.

Do not use on damaged or broken skin.

When using this product keep out of eyes. Rinse with water to remove.

Stop use and ask a doctor if rash occurs.

If swallowed, get medical help or contact poison control center

Keep out of reach of children

INACTIVE INGREDIENT

Purified Water, Capric/Caprylic, Glycerin, Cetearyl Alcohol, Ceteareth-20, Cyclopentasiloxane, Cyclotetrasiloxane, Dimethilconol, Potassium Cetyl Phosphate, Glyceryl Stearate, PEG-100 Stearate, Acrylate Copolymer, Phenoxyethanol, Ethylhexylglycerin, Helianthus annuus (Sunflower) Seed Oil, Carthamus tinctorius (Safflower) Seed Oil, Vitis vinifera (Grape) Seed Oil, Allantoin, Hyaluronic acid, Oenothera Biennis (Evening Primrose) Borago officinalis (Starflower) Oil, Rubus idaeus (Red Raspberry) Seed Oil, Bisobolol (Chamomile)

DOSAGE AND ADMINISTRATION

Apply liberally to dry skin 15 minutes before sun exposure *Reapply to dry skin after 80 minutes of swimming or sweating *immediately after towel drying * at least every 2 hours * Children under 6 months ask a doctor

OTHER iNFORMATION Protect the product in this container from excessive heat and direct sun.

OTHER SAFETY INFORMATION

Sun Protection Measures Spending time in the sun increases your risk of skin cancer and early skin aging. To decrease this risk, regularly use a sunscreen with a broad spectrum SPF value of 15 or higher and other sun protection measures, including * Limit time in the sun, especially from 10a.m. – 2 p.m. * Wear long-sleeved shirts, pants, hats, and sunglasses